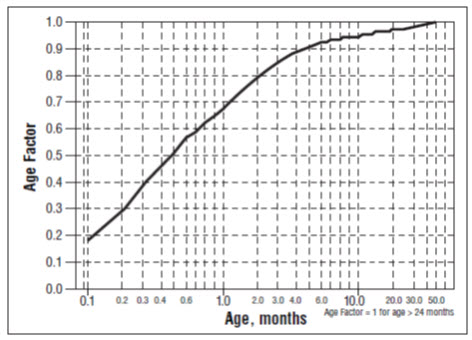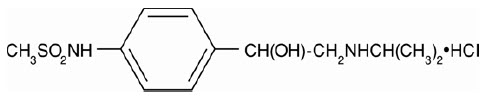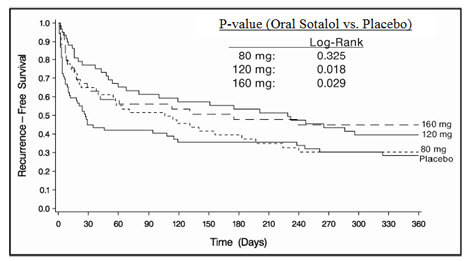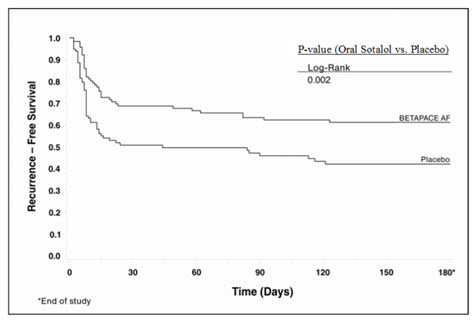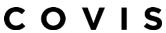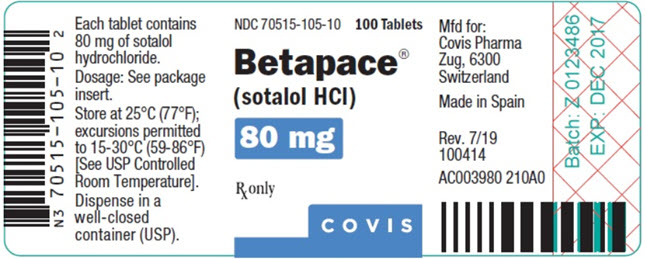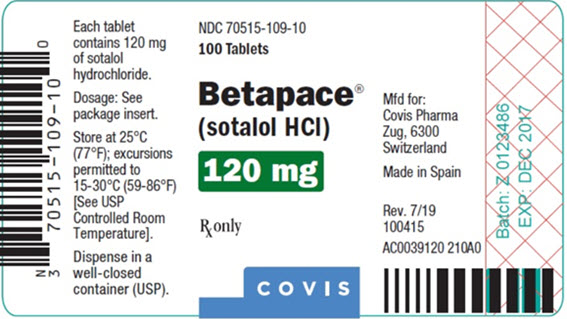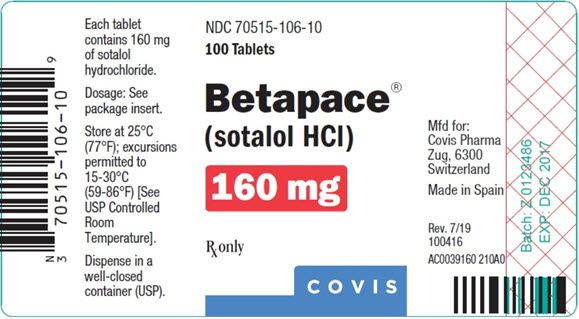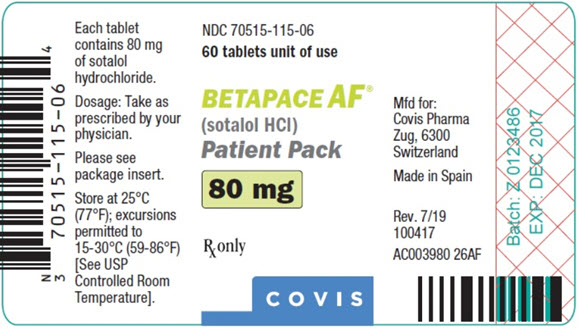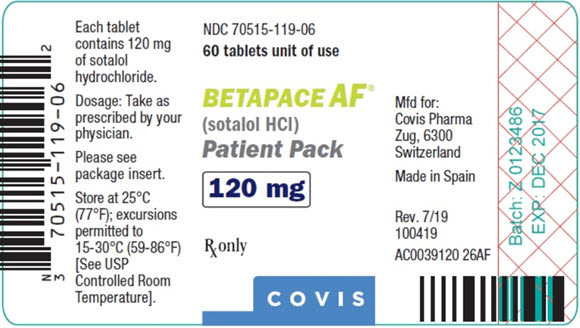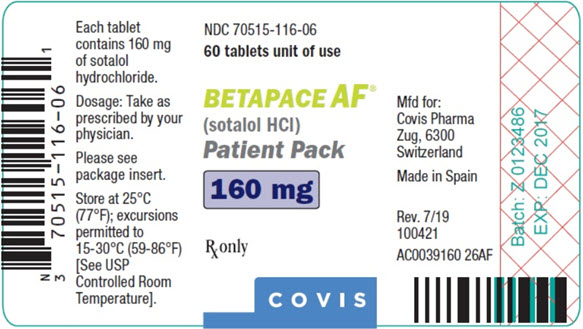 DRUG LABEL: BETAPACE
NDC: 70515-105 | Form: TABLET
Manufacturer: Covis Pharma US, Inc
Category: prescription | Type: HUMAN PRESCRIPTION DRUG LABEL
Date: 20230615

ACTIVE INGREDIENTS: SOTALOL HYDROCHLORIDE 80 mg/1 1
INACTIVE INGREDIENTS: MICROCRYSTALLINE CELLULOSE; LACTOSE, UNSPECIFIED FORM; STARCH, CORN; STEARIC ACID; MAGNESIUM STEARATE; SILICON DIOXIDE; FD&C BLUE NO. 2

HIGHLIGHTS OF PRESCRIBING INFORMATION

These highlights do not include all the information needed to use BETAPACE®/BETAPACE AF safely and effectively. See full prescribing information for BETAPACE/BETAPACE AF.
BETAPACE (sotalol hydrochloride) tablets, for oral use
BETAPACE AF (sotalol hydrochloride) tablets, for oral use
Initial U.S. Approval: 1992

WARNING: LIFE-THREATENING PROARRHYTHMIA

See full prescribing information for complete boxed warning.

- Betapace/Betapace AF can cause life-threatening ventricular tachycardia associated with QT interval prolongation.
- If the QT interval prolongs to 500 msec or greater, reduce the dose, lengthen the dosing interval, or discontinue the drug.
- Initiate or reinitiate in a facility that can provide cardiac resuscitation and continuous electrocardiographic monitoring.
- Adjust the dosing interval based on creatinine clearance.

1 INDICATIONS AND USAGE

Betapace/Betapace AF is an antiarrhythmic indicated for:

- the treatment of life-threatening ventricular arrhythmias (1.1)
- the maintenance of normal sinus rhythm in patients with atrial fibrillation or flutter (AFIB/AFL) (1.2)

Limitations of Use

- Betapace has not been shown to enhance survival in patients with life threatening ventricular arrhythmias (1.1)
- Avoid use in patients with minimally symptomatic or easily reversible AFIB/AFL (1.2)

2 DOSAGE AND ADMINISTRATION

- Betapace/Betapace AF: Initial dosage in adults is 80 mg twice daily. Increase the dose as needed in increments of 80 mg/day, every 3 days to a maximum 320 mg total daily dose (2.2)
- Pediatrics: Dosage depends on age (2.4)

3 DOSAGE FORMS AND STRENGTHS

80 mg, 120 mg and 160 mg tablets (3)

4 CONTRAINDICATIONS

For the treatment of AFIB/AFL or ventricular arrhythmias

- Sinus bradycardia, 2nd or 3rd degree AV block, sick sinus syndrome (4)
- Congenital or acquired long QT syndrome (4)
- Serum potassium <4 mEq/L (4)
- Cardiogenic shock, decompensated heart failure (4)
- Bronchial asthma or related bronchospastic conditions (4)
- Hypersensitivity to sotalol (4)

For the treatment of AFIB/AFL also contraindicated for:

- QT interval >450 msec (4)

5 WARNINGS AND PRECAUTIONS

- QT prolongation, bradycardia, AV block, hypotension, worsening heart failure: Reduce dose or discontinue (5.1)
- Correct any electrolyte disturbances (5.1)
- Acute exacerbation of coronary artery disease upon cessation of therapy: Do not abruptly discontinue (5.5)
- Diabetes: May mask symptoms of hypoglycemia and alter glucose levels; monitor (5.7)

6 ADVERSE REACTIONS

The most common adverse reactions (≥2%) for Betapace are: fatigue 4%, bradycardia (less than 50 bpm) 3%, dyspnea 3%, proarrhythmia 3%, asthenia 2%, and dizziness 2%. (6)

To report SUSPECTED ADVERSE REACTIONS, contact Covis Pharma at 1-866-488-4423 or FDA at 1-800-FDA-1088 or www.fda.gov/medwatch.

7 DRUG INTERACTIONS

- Class I or III Antiarrhythmics or other drugs that prolong the QT interval: Avoid concomitant use (7.1)
- Digoxin, calcium channel blocker: increased risk of bradycardia, hypotension, heart failure (7.2)
- Dosage of insulin or antidiabetic drugs may need adjustment (7.5)
- Aluminum- or magnesium-based antacids reduce sotalol exposure (7.7)

8 USE IN SPECIFIC POPULATIONS

- Lactation: Do not breastfeed (8.2)

FULL PRESCRIBING INFORMATION

WARNING: LIFE-THREATENING PROARRHYTHMIA

To minimize the risk of drug-induced arrhythmia, initiate or reinitiate oral sotalol in a facility that can provide cardiac resuscitation and continuous electrocardiographic monitoring.

Sotalol can cause life-threatening ventricular tachycardia associated with QT interval prolongation.

If the QT interval prolongs to 500 msec or greater, reduce the dose, lengthen the dosing interval, or discontinue the drug.

Calculate creatinine clearance to determine appropriate dosing [see Dosage and Administration (2.5)].

1 INDICATIONS AND USAGE

1.1 Life-Threatening Ventricular Arrhythmias

Betapace/Betapace AF is indicated for the treatment of documented, life-threatening ventricular arrhythmias, such as sustained ventricular tachycardia (VT).

Limitation of Use:

Betapace/Betapace AF has not been shown to enhance survival in patients with life-threatening ventricular arrhythmias.

1.2 Delay in Recurrence of Atrial Fibrillation/Atrial Flutter (AFIB/AFL)

Betapace/Betapace AF is indicated for the maintenance of normal sinus rhythm (delay in time to recurrence of AFIB/AFL) in patients with highly symptomatic AFIB/AFL who are currently in sinus rhythm.

Limitation of Use:

Because Betapace/Betapace AF can cause life-threatening ventricular arrhythmias, reserve its use for patients in whom AFIB/AFL is highly symptomatic. Patients with paroxysmal AFIB that is easily reversed (by Valsalva maneuver, for example) should usually not be given Betapace/Betapace AF.

2 DOSAGE AND ADMINISTRATION

2.1 General Safety Measures for Initiation of Oral Sotalol Therapy

Withdraw other antiarrhythmic therapy before starting Betapace/Betapace AF and monitor for a minimum of 2 to 3 plasma half-lives prior to initiating Betapace/Betapace AF therapy if the patient's clinical condition permits [see Drug Interactions (7)].

Hospitalize patients being initiated or re-initiated on sotalol for at least 3 days or until steady-state drug levels are achieved, in a facility that can provide cardiac resuscitation and continuous electrocardiographic monitoring. Initiate oral sotalol therapy in the presence of personnel trained in the management of serious arrhythmias. Perform a baseline ECG to determine the QT interval and measure and normalize serum potassium and magnesium levels before initiating therapy. Measure serum creatinine and calculate an estimated creatinine clearance in order to establish the appropriate dosing interval. Monitor QTc 2 to 4 hours after each uptitration in dose.

Discharge patients on sotalol therapy from an in-patient setting with an adequate supply of sotalol to allow uninterrupted therapy until the patient can fill a sotalol prescription.

Advise patients who miss a dose to take the next dose at the usual time. Do not double the dose or shorten the dosing interval.

2.2 Adult Dose for Ventricular Arrhythmias

The recommended initial dose is 80 mg twice daily. This dose may be increased in increments of 80 mg per day every 3 days provided the QTc <500 msec [see Warnings and Precautions (5.1)]. Continually monitor patients until steady state blood levels are achieved. In most patients, a therapeutic response is obtained at a total daily dose of 160 to 320 mg/day, given in two or three divided doses. Oral doses as high as 480 to 640 mg/day have been utilized in patients with refractory life-threatening arrhythmias.

2.3 Adult Dose for Prevention of Recurrence of AFIB/AFL

The recommended initial dose is 80 mg twice daily. This dose may be increased in increments of 80 mg per day every 3 days provided the QTc <500 msec [see Warnings and Precautions (5.1)]. Continually monitor patients until steady state blood levels are achieved. Most patients will have satisfactory response with 120 mg twice daily. Initiation of sotalol in patients with QTc >450 msec is contraindicated [see Contraindication (4)].

2.4 Pediatric Dose for Ventricular Arrhythmias or AFIB/AFL

Use the same precautionary measures for children as you would use for adults when initiating and re-initiating sotalol treatment.

For Children Aged About 2 Years and Older

For children aged about 2 years and older, with normal renal function, doses normalized for body surface area are appropriate for both initial and incremental dosing. Since the Class III potency in children is not very different from that in adults, reaching plasma concentrations that occur within the adult dose range is an appropriate guide [see Clinical Pharmacology (12.1, 12.3)].

For initiation of treatment, 1.2 mg/kg three times a day (3.6 mg/kg total daily dose) is approximately equivalent to the initial 160 mg total daily dose for adults. Subsequent titration to a maximum of 2.4 mg/kg three times a day (approximately equivalent to the 360 mg total daily dose for adults) can then occur. Titration should be guided by clinical response, heart rate, and QTc, with increased dosing being preferably conducted in-hospital. Allow at least 36 hours between dose increments to attain steady-state plasma concentrations of sotalol in patients with age‑adjusted normal renal function.

For Children Aged About 2 Years or Younger

For children aged about 2 years or younger, the pediatric dosage should be reduced by a factor that depends upon age, as shown in the following graph (age plotted on a logarithmic scale in months):

For a child aged 1 month, multiply the starting dose by 0.7; the initial starting dose would be (1.2 mg/kg X 0.7)=0.8 mg/kg, administered three times daily. For a child aged about 1 week, multiply the initial starting dose by 0.3; the starting dose would be (1.2 mg/kg X 0.3)=0.4 mg/kg. Use similar calculations for dose titration.

2.5 Dosage for Patients with Renal Impairment

Adults

In any age group with decreased renal function, sotalol doses should be lowered or the intervals

between doses increased. It will take much longer to reach steady-state with any dose and/or frequency of administration. Closely monitor heart rate and QTc.

Dose escalations in renal impairment should be done after administration of at least 5 doses at appropriate intervals (Table 1). Sotalol is partly removed by dialysis; specific advice is unavailable on dosing patients on dialysis.

Administer the initial dose of 80 mg and subsequent doses at the intervals listed in Table 1.

Table 1 Dosing Intervals in Renal Impairment
Creatinine Clearance mL/min | Dosing Interval (hours)
>60 | 12
30–59 | 24
10–29 | 36–48
<10 | Dose should be individualized

2.6 Preparation of Extemporaneous Oral Solution

Betapace/Betapace AF Syrup 5 mg/mL can be compounded using Simple Syrup containing 0.1% sodium benzoate (Syrup, NF) as follows:

1. Measure 120 mL of Simple Syrup.
2. Transfer the syrup to a 6-ounce amber plastic (polyethylene terephthalate [PET]) prescription bottle. An oversized bottle is used to allow for a headspace, so that there will be more effective mixing during shaking of the bottle.
3. Add five (5) Betapace/Betapace AF 120 mg tablets to the bottle. These tablets are added intact; it is not necessary to crush the tablets. The addition of the tablets can also be done first. The tablets can also be crushed, if preferred. If the tablets are crushed, take care to transfer the entire quantity of tablet powder into the bottle containing the syrup.
4. Shake the bottle to wet the entire surface of the tablets. If the tablets have been crushed, shake the bottle until the endpoint is achieved.
5. Allow the tablets to hydrate for at least two hours.
6. After at least two hours have elapsed, shake the bottle intermittently over the course of at least another two hours until the tablets are completely disintegrated. The tablets can be allowed to hydrate overnight to simplify the disintegration process.

The endpoint is achieved when a dispersion of fine particles in the syrup is obtained.

This compounding procedure results in a solution containing 5 mg/mL of sotalol HCl. The fine solid particles are the water-insoluble inactive ingredients of the tablets.

Stability studies indicate that the suspension is stable for three months when stored at 15°C to 30°C (59°F to 86°F) [see USP Controlled Room Temperature] and ambient humidity.

3 DOSAGE FORMS AND STRENGTHS

Betapace is supplied as capsule-shaped, light-blue, scored tablets:

- 80 mg imprinted with “BETAPACE” on one side and 80 mg on the other
- 120 mg imprinted with “BETAPACE” on one side and 120 mg on the other
- 160 mg imprinted with “BETAPACE” on one side and 160 mg on the other

Betapace AF is supplied as capsule-shaped, white scored tablet:

- 80 mg imprinted with “BHCP” on one side and 80 mg on the other
- 120 mg imprinted with “BHCP” on one side and 120 mg on the other
- 160 mg imprinted with “BHCP” on one side and 160 mg on the other

4 CONTRAINDICATIONS

Betapace/Betapace AF is contraindicated in patients with:

- Sinus bradycardia, sick sinus syndrome, second and third degree AV block, unless a functioning pacemaker is present
- Congenital or acquired long QT syndromes
- Cardiogenic shock or decompensated heart failure
- Serum potassium <4 mEq/L
- Bronchial asthma or related bronchospastic conditions
- Hypersensitivity to sotalol

For the treatment of AFIB/AFL, Betapace/Betapace AF is also contraindicated in patients with:

- Baseline QT interval >450 msec

5 WARNINGS AND PRECAUTIONS

5.1 QT Prolongation and Proarrhythmia

Betapace/Betapace AF can cause serious and potentially fatal ventricular arrhythmias such as sustained VT/VF, primarily Torsade de Pointes (TdP) type ventricular tachycardia, a polymorphic ventricular tachycardia associated with QT interval prolongation. Factors such as reduced creatinine clearance, female sex, higher doses, reduced heart rate, and history of sustained VT/VF or heart failure increase the risk of TdP. The risk of TdP can be reduced by adjustment of the sotalol dose according to creatinine clearance and by monitoring the ECG for excessive increases in the QT interval [see Dosage and Administration (2.1)].

Correct hypokalemia or hypomagnesemia prior to initiating Betapace/Betapace AF, as these conditions can exaggerate the degree of QT prolongation, and increase the potential for Torsade de Pointes. Special attention should be given to electrolyte and acid-base balance in patients experiencing severe or prolonged diarrhea or patients receiving concomitant diuretic drugs.

Proarrhythmic events must be anticipated not only on initiating therapy, but with every upward dose adjustment [see Dosage and Administration (2.1)].

Avoid use with other drugs known to cause QT prolongation [see Drug Interactions (7.1)].

5.2 Bradycardia/Heart Block/Sick Sinus Syndrome

Sinus bradycardia (heart rate less than 50 bpm) occurred in 13% of patients receiving sotalol in clinical trials, and led to discontinuation in about 3% of patients. Bradycardia itself increases the risk of Torsade de Pointes. Sinus pause, sinus arrest and sinus node dysfunction occur in less than 1% of patients. The incidence of 2nd- or 3rd-degree AV block is approximately 1%.

Betapace/Betapace AF is contraindicated in patients with sick sinus syndrome because it may cause sinus bradycardia, sinus pauses, or sinus arrest.

5.3 Hypotension

Sotalol produces significant reductions in both systolic and diastolic blood pressures and may result in hypotension. Monitor hemodynamics in patients with marginal cardiac compensation.

5.4 Heart Failure

New onset or worsening heart failure may occur during initiation or uptitration of sotalol because of its beta-blocking effects. Monitor for signs and symptoms of heart failure and discontinue treatment if symptoms occur.

5.5 Cardiac Ischemia after Abrupt Discontinuation

Following abrupt cessation of therapy with beta-adrenergic blockers, exacerbations of angina pectoris and myocardial infarction may occur. When discontinuing chronically administered Betapace/Betapace AF, particularly in patients with ischemic heart disease, gradually reduce the dosage over a period of 1 to 2 weeks, if possible, and monitor the patient. If angina markedly worsens or acute coronary ischemia develops, treat appropriately and consider use of an alternative beta-blocker. Warn patients not to interrupt therapy without their physician’s advice. Because coronary artery disease is common, but may be unrecognized, the abrupt discontinuation of sotalol may unmask latent coronary insufficiency.

5.6 Bronchospasm

Patients with bronchospastic diseases (for example chronic bronchitis and emphysema) should not receive beta-blockers. If Betapace/Betapace AF is to be administered, use the smallest effective dose, to minimize inhibition of bronchodilation produced by endogenous or exogenous catecholamine stimulation of beta-2-receptors.

5.7 Effects on Blood Sugar

Beta-blockers may prevent early warning signs of hypoglycemia, such as tachycardia, and increase the risk for severe or prolonged hypoglycemia at any time during treatment, especially in patients with diabetes mellitus or children and patients who are fasting (i.e., surgery, not eating regularly, or are vomiting). If severe hypoglycemia occurs, patients should be instructed to seek emergency treatment. Elevated blood glucose levels and increased insulin requirements can occur in diabetic patients.

5.8 Thyroid Abnormalities

Avoid abrupt withdrawal of beta-blockade in patients with thyroid disease because it may lead to an exacerbation of symptoms of hyperthyroidism, including thyroid storm. Beta-blockade may mask certain clinical signs (for example, tachycardia) of hyperthyroidism.

5.9 Anaphylaxis

While taking beta-blockers, patients with a history of anaphylactic reaction to a variety of allergens may have a more severe reaction on repeated challenge, either accidental, diagnostic, or therapeutic. Such patients may be unresponsive to the usual doses of epinephrine used to treat the allergic reaction.

5.10 Major Surgery

Chronically administered beta-blocking therapy should not be routinely withdrawn prior to major surgery; however, the impaired ability of the heart to respond to reflex adrenergic stimuli may augment the risks of general anesthesia and surgical procedures.

6 ADVERSE REACTIONS

6.1 Clinical Trials Experience

Because clinical trials are conducted under widely varying conditions, adverse reaction rates observed in the clinical trials of a drug cannot be directly compared to rates in the clinical trials of another drug and may not reflect the rates observed in practice.

Adverse reactions that are clearly related to sotalol are those that are typical of its Class II (beta-blocking) and Class III (cardiac action potential duration prolongation) effects and are dose related.

Ventricular Arrhythmias

Serious Adverse Reactions

Betapace/Betapace AF can cause serious and potentially fatal ventricular arrhythmias such as sustained VT/VF, primarily Torsade de Pointes (TdP) [see Warnings and Precautions (5.1)]. The effect on QT and the risk of Torsade de Pointes are both dose related.

Pediatric Patients

In an unblinded multicenter trial of 25 pediatric patients aged ≤ 1 month to 12 years with SVT and/or VT receiving daily doses of 30, 90, and 210 mg/m2 with dosing every 8 hours for a total of 9 doses, no Torsade de Pointes or other serious new arrhythmias were observed. The clinical trial safety profile in pediatric patients was similar to that in adult patients. Both the Class III and beta-blocking effects of sotalol were linearly related to the plasma concentration [see Clinical Pharmacology (12.2)].

Atrial Fibrillation/Atrial Flutter

Placebo-controlled Clinical Trials

In a pooled clinical trial population consisting of 4 placebo-controlled studies with 275 patients with atrial fibrillation (AFIB)/atrial flutter (AFL) treated with 160 to 320 mg of Betapace AF, the following adverse reactions presented in Table 2 occurred in at least 2% of placebo-treated patients and at a lesser rate than Betapace-treated patients. The data are presented by incidence of reactions in the Betapace AF and placebo groups by body system and daily dose.

Table 2: Incidence (%) of Common Adverse Reactions (≥ 2% in the Placebo Group and Less Frequent Than in the Betapace AF Groups) in Four Placebo-controlled Studies of Patients with AFIB/AFL
Adverse Reaction | Placebo | Betapace AF Total Daily Dose
Adverse Reaction | N = 282 (%) | 160-240 mg N = 153 (%) | >240-320 mg N = 122 (%)
Bradycardia | 3 | 13 | 12
Diarrhea | 2 | 5 | 6
Nausea/Vomiting | 5 | 8 | 6
Fatigue | 9 | 20 | 19
Hyperhidrosis | 3 | 5 | 5
Weakness | 3 | 5 | 5
Dizziness | 12 | 16 | 13
Headache | 5 | 3 | 12
Dyspnea | 7 | 9 | 10

Overall, discontinuation because of unacceptable adverse events was necessary in 17% of the patients, and occurred in 10% of patients less than two weeks after starting treatment. The most common adverse reactions leading to discontinuation of Betapace AF were: fatigue 4.6%, bradycardia 2.4%, proarrhythmia 2.2%, dyspnea 2%, and QT interval prolongation 1.4%.

6.2 Postmarketing Experience

The following adverse drug reactions have been identified during post-approval use of sotalol. Because these reactions are reported voluntarily from a population of uncertain size, it is not always possible to reliably estimate their frequency or establish a causal relationship to drug exposure: emotional lability, slightly clouded sensorium, incoordination, vertigo, paralysis, thrombocytopenia, eosinophilia, leukopenia, photosensitivity reaction, fever, pulmonary edema, hyperlipidemia, myalgia, pruritis, and alopecia.

7 DRUG INTERACTIONS

7.1 Antiarrhythmics and Other QT Prolonging Drugs

Discontinue Class I or Class III antiarrhythmic agents for at least three half-lives prior to dosing with sotalol. Class Ia antiarrhythmic drugs, such as disopyramide, quinidine, and procainamide, and other Class III drugs (for example, amiodarone) are not recommended as concomitant therapy with Betapace/Betapace AF, because of their potential to prolong refractoriness [see Warnings and Precautions (5.2)].

7.2 Negative Chronotropes

Digitalis glycosides, diltiazem, verapamil, and beta-blockers slow atrioventricular conduction and decrease heart rate. Concomitant use with negative chronotropes can increase the risk of bradycardia or hypotension.

7.3 Catecholamine-Depleting Agents

Concomitant use of catecholamine-depleting drugs, such as reserpine and guanethidine, with a beta-blocker may produce an excessive reduction of resting sympathetic nervous tone. Monitor such patients for evidence of hypotension and/or marked bradycardia which may produce syncope.

7.4 Insulin and Oral Antidiabetics

Hyperglycemia may occur, and the dosage of insulin or antidiabetic drugs may require adjustment [see Warnings and Precautions (5.7)].

7.5 Beta-2-Receptor Stimulants

Beta-agonists such as albuterol, terbutaline and isoproterenol may have to be administered in increased dosages when used concomitantly with sotalol.

7.6 Clonidine

Concomitant use with sotalol increases the risk of bradycardia and AV block. Because beta-blockers may potentiate the rebound hypertension sometimes observed after clonidine discontinuation, withdraw sotalol several days before the gradual withdrawal of clonidine to reduce the risk of rebound hypertension.

7.7 Antacids

Avoid administration of oral sotalol within 2 hours of antacids containing aluminum oxide and magnesium hydroxide.

7.8 Drug/Laboratory Test Interactions

The presence of sotalol in the urine may result in falsely elevated levels of urinary metanephrine when measured by fluorimetric or photometric methods.

8 USE IN SPECIFIC POPULATIONS

8.1 Pregnancy

Risk Summary

Both the untreated underlying condition in pregnancy and the use of sotalol in pregnancy cause adverse outcomes to the mother and fetus/neonate (see Clinical Considerations). In animal reproduction studies in rats, early resorptions were increased at 15 times the maximum recommended human dose (MRHD). In rabbits an increase in fetal death was observed at 2 times the MRHD administered as a single dose. Sotalol did not reveal any teratogenic potential in rats or rabbits at 15 and 2 times the MRHD respectively (see Data).

All pregnancies have a background risk of birth defect, loss, or other adverse outcomes. The estimated background risk of major birth defects and miscarriage for the indicated population is unknown. In the United States (U.S.) general population, the estimated background risk of major birth defects and miscarriage in clinically recognized pregnancies is 2% to 4% and 15% to 20%, respectively.

Clinical Considerations

The incidence of VT is increased and may be more symptomatic during pregnancy. Most tachycardia episodes are initiated by ectopic beats and the occurrence of arrhythmia episodes may, therefore, increase during pregnancy. Breakthrough arrhythmias may also occur during pregnancy, as therapeutic treatment levels may be difficult to maintain due to the increased volume of distribution and increased drug metabolism inherent in the pregnant state.

Fetal/Neonatal Adverse Reactions

Sotalol has been shown to cross the placenta and is found in amniotic fluid. From published observational studies, the potential fetal adverse effects of sotalol use during pregnancy are growth restriction, transient fetal bradycardia, hyperbilirubinemia, hypoglycemia, uterine contractions, and possible intrauterine death. Sotalol may have a greater effect on QT prolongation in the immature heart than in the adult heart, and therefore, conveys an increased risk of serious fetal arrhythmia and/or possible intrauterine death. Monitor the newborn for symptoms of beta blockade.

Labor or Delivery

Generally, risk of arrhythmias increases during the labor and delivery process; therefore, considering the proarrhythmia potential of the drug, patients treated with sotalol should be monitored continuously during labor and delivery.

Data

Animal Data

Reproduction studies in rats and rabbits administered sotalol during organogenesis at 15 times and 2 times the MRHD as mg/m^2, respectively, did not reveal any teratogenic potential associated with sotalol.

In pregnant rats, sotalol doses administered during organogenesis at approximately 15 times the MRHD as mg/m^2, increased the number of early resorptions, while no increase in early resorptions was noted at 2 times the MRHD as mg/m^2.

In reproductive studies in rabbits, a sotalol dose (160 mg/kg/day) at 5 times the MRHD as mg/m2 produced a slight increase in fetal death, and maternal toxicity. However, one study from published data reported an increase in fetal deaths in rabbits receiving a single dose (50 mg/kg) at 2 times the MRHD as mg/m^2 on gestation day 14.

8.2 Lactation

Risk Summary

Limited available data from published literature report that sotalol is present in human milk. The estimated daily infant dose of sotalol received from breastmilk is 0.8-3.4 mg/kg, estimated at 22 to 25.5% of the maternal weight-adjusted dosage of Betapace (see Data). The amount of the drug in breast milk is similar to the neonatal therapeutic dosage. Therefore, there is potential for bradycardia and other symptoms of beta blockade such as dry mouth, skin or eyes, diarrhea or constipation in the breastfed infant. There is no information regarding the effects of sotalol on milk production. Because of the potential serious adverse reactions to the breastfed child and the high level of sotalol in breast milk, advise women not to breastfeed while on treatment with Betapace.

Data

Sotalol is present in human milk in high levels. A prospective study evaluated 20 paired samples of breast milk and maternal blood from 5 mothers who elected to breastfeed. Breast milk samples had a mean sotalol concentration of 10.5 µg/mL (± 1.1 µg/mL; range: 4.8 to 20.2 µg/mL) compared to a simultaneous mean maternal plasma concentration of 2.3 µg/mL (± 0.3 µg/mL; range: 0.8 to 5.0 µg/mL). The mean milk plasma ratio was 5.4:1 (range: 2.2 to 8.8). The estimated daily infant dose was 0.8-3.4 mg/kg, estimated at 22 to 25.5% of the maternal weight-adjusted dosage of sotalol. This is similar to recommended therapeutic dose in neonates. None of the mothers reported any adverse reactions in the breastfed infant.

8.3 Females and Males of Reproductive Potential

Infertility

Based on the published literature, beta blockers (including sotalol) may cause erectile dysfunction.

8.4 Pediatric Use

The safety and effectiveness of sotalol in children have not been established. However, the Class III electrophysiologic and beta-blocking effects, the pharmacokinetics, and the relationship between the effects (QTc interval and resting heart rate) and drug concentrations have been evaluated in children aged between 3 days and 12 years old [see Dosage and Administration (2.4) and Clinical Pharmacology (12.2)].

Associated side effects of sotalol use in pediatric patients are those typical of a beta-blocking agent, and lead to discontinuation of the drug in 3 to 6% of patients. As in adults, the Class III antiarrhythmic action of sotalol in pediatric patients is associated with a significant proarrhythmic potential for adverse effects. In pediatric patients, the incidence of proarrhythmic side effects of sotalol varies from 0 to 22%; however, sotalol-induced Torsade de Pointes tachycardias are observed less frequently in the pediatric population.

Proarrhythmic effects of sotalol in pediatric patients included increased ventricular ectopy and exacerbation of bradycardia, the latter predominantly in patients sinus node dysfunction following surgery for congenital cardiac defects. Bradycardia may require emergency pacemaker implantation. Close in-patient monitoring is recommended for several days.

8.6 Renal Impairment

Sotalol is mainly eliminated via the kidneys. Adjust dosing intervals based on creatinine clearance [see Dosage and Administration (2.5)].

10 OVERDOSAGE

Intentional or accidental overdosage with sotalol has resulted in death.

Symptoms and Treatment of Overdosage

The most common signs to be expected are bradycardia, congestive heart failure, hypotension, bronchospasm, and hypoglycemia. In cases of massive intentional overdosage (2 to 16 grams) of sotalol the following clinical findings were seen: hypotension, bradycardia, cardiac asystole, prolongation of QT interval, Torsade de Pointes, ventricular tachycardia, and premature ventricular complexes. If overdosage occurs, therapy with sotalol should be discontinued and the patient observed closely. Because of the lack of protein binding, hemodialysis is useful for reducing sotalol plasma concentrations. Patients should be carefully observed until QT intervals are normalized and the heart rate returns to levels >50 bpm.

The occurrence of hypotension following an overdose may be associated with an initial slow drug elimination phase (half-life of 30 hours) thought to be due to a temporary reduction of renal function caused by the hypotension. In addition, if required, the following therapeutic measures are suggested:

Bradycardia or Cardiac Asystole: Atropine, another anticholinergic drug, a beta-adrenergic agonist, or transvenous cardiac pacing.

Heart Block: (second and third degree) transvenous cardiac pacemaker.

Hypotension: (depending on associated factors) epinephrine rather than isoproterenol or norepinephrine may be useful.

Bronchospasm: Aminophylline or aerosol beta-2-receptor stimulant. Higher than normal doses of beta-2-receptor stimulants may be required.

Torsade de Pointes: DC cardioversion, transvenous cardiac pacing, epinephrine, magnesium sulfate.

11 DESCRIPTION

Betapace/Betapace AF contains sotalol hydrochloride, an antiarrhythmic drug with Class II (beta-adrenoreceptor blocking) and Class III (cardiac action potential duration prolongation) properties. Betapace is supplied as a light-blue, capsule-shaped tablet for oral administration. Betapace AF is supplied as a white, capsule-shaped tablet for oral administration. Sotalol hydrochloride is a white, crystalline solid with a molecular weight of 308.8. It is hydrophilic, soluble in water, propylene glycol, and ethanol, but is only slightly soluble in chloroform. Chemically, sotalol hydrochloride is d,l-N-[4-[1-hydroxy-2-[(1-methylethyl) amino]ethyl]phenyl]methane-sulfonamide monohydrochloride. The molecular formula is C12H20N2O3 S·HCl and is represented by the following structural formula:

Betapace Tablets contain the following inactive ingredients: microcrystalline cellulose, lactose, starch, stearic acid, magnesium stearate, colloidal silicon dioxide, and FD&C blue color #2 (aluminum lake, conc.).

Betapace AF Tablets contain the following inactive ingredients: microcrystalline cellulose, lactose, starch, stearic acid, magnesium stearate, and colloidal silicon dioxide.

12 CLINICAL PHARMACOLOGY

12.1 Mechanism of Action

Sotalol has both beta-adrenoreceptor blocking (Vaughan Williams Class II) and cardiac action potential duration prolongation (Vaughan Williams Class III) antiarrhythmic properties. The two isomers of sotalol have similar Class III antiarrhythmic effects, while the l-isomer is responsible for virtually all of the beta-blocking activity. The beta-blocking effect of sotalol is non-cardioselective, half maximal at about 80 mg/day and maximal at doses between 320 and 640 mg/day. Sotalol does not have partial agonist or membrane stabilizing activity. Although significant beta-blockade occurs at oral doses as low as 25 mg, significant Class III effects are seen only at daily doses of 160 mg and above.

In children, a Class III electrophysiologic effect can be seen at daily doses of 210 mg/m^2 body surface area (BSA). A reduction of the resting heart rate due to the beta-blocking effect of sotalol is observed at daily doses ≥90 mg/m^2 in children.

12.2 Pharmacodynamics

Cardiac Electrophysiological Effects

Sotalol hydrochloride prolongs the plateau phase of the cardiac action potential in the isolated myocyte, as well as in isolated tissue preparations of ventricular or atrial muscle (Class III activity). In intact animals it slows heart rate, decreases AV nodal conduction, and increases the refractory periods of atrial and ventricular muscle and conduction tissue.

In man, the Class II (beta-blockade) electrophysiological effects of sotalol are manifested by increased sinus cycle length (slowed heart rate), decreased AV nodal conduction and increased AV nodal refractoriness. The Class III electrophysiological effects in man include prolongation of the atrial and ventricular monophasic action potentials, and effective refractory period prolongation of atrial muscle, ventricular muscle, and atrio-ventricular accessory pathways (where present) in both the anterograde and retrograde directions. With oral doses of 160 to 640 mg/day, the surface ECG shows dose-related mean increases of 40 to 100 msec in QT and 10 to 40 msec in QTc [see Warnings and Precautions (5.1)]. No significant alteration in QRS interval is observed.

In a small study (n=25) of patients with implanted defibrillators treated concurrently with Betapace, the average defibrillatory threshold was 6 joules (range: 2 to 15 joules) compared to a mean of 16 joules for a nonrandomized comparative group primarily receiving amiodarone.

Twenty-five children in an unblinded, multicenter trial with SVT and/or ventricular tachyarrhythmias, aged between 3 days and 12 years (mostly neonates and infants), received an ascending titration regimen with daily doses of 30, 90, and 210 mg/m^2 with dosing every 8 hours for a total 9 doses. During steady-state, the respective average increases above baseline of the QTc interval were 2, 14, and 29 msec at the 3 dose levels. The respective mean maximum increases above baseline of the QTc interval were 23, 36, and 55 msec at the 3 dose levels. The steady-state percent increases in the RR interval were 3, 9, and 12%. The smallest children (BSA<0.33 m^2) showed a tendency for larger Class III effects (ΔQTc) and an increased frequency of prolongations of the QTc interval as compared with larger children (BSA≥0.33 m^2). The beta-blocking effects also tended to be greater in the smaller children (BSA<0.33 m^2). Both the Class III and beta-blocking effects of sotalol were linearly related to the plasma concentrations.

Hemodynamics

In a study of systemic hemodynamic function measured invasively in 12 patients with a mean LV ejection fraction of 37% and ventricular tachycardia (9 sustained and 3 non-sustained), a median dose of 160 mg twice daily of Betapace produced a 28% reduction in heart rate and a 24% decrease in cardiac index at 2 hours post-dosing at steady-state. Concurrently, systemic vascular resistance and stroke volume showed nonsignificant increases of 25% and 8%, respectively. One patient was discontinued because of worsening congestive heart failure. Pulmonary capillary wedge pressure increased significantly from 6.4 mmHg to 11.8 mmHg in the 11 patients who completed the study. Mean arterial pressure, mean pulmonary artery pressure and stroke work index did not significantly change. Exercise and isoproterenol induced tachycardia are antagonized by Betapace, and total peripheral resistance increases by a small amount.

In hypertensive patients, sotalol produces significant reductions in both systolic and diastolic blood pressures. Although sotalol is usually well-tolerated hemodynamically, deterioration in cardiac performance may occur in patients with marginal cardiac compensation [see Warnings and Precautions (5.3)].

12.3 Pharmacokinetics

The pharmacokinetics of the d- and l-enantiomers of sotalol are essentially identical.

Absorption

In healthy subjects, the oral bioavailability of sotalol is 90 to 100%. After oral administration, peak plasma concentrations are reached in 2.5 to 4 hours, and steady-state plasma concentrations are attained within 2 to 3 days (that is, after 5 to 6 doses when administered twice daily). Over the dosage range 160 to 640 mg/day, sotalol displays dose proportionality with respect to plasma concentrations. When administered with a standard meal, the absorption of sotalol was reduced by approximately 20% compared to administration in fasting state.

Distribution

Sotalol does not bind to plasma proteins. Distribution occurs to a central (plasma) and to a peripheral compartment. Sotalol crosses the blood brain barrier poorly.

Metabolism

Sotalol is not metabolized and is not expected to inhibit or induce any CYP450 enzymes.

Excretion

Excretion of sotalol is predominantly via the kidney in the unchanged form, and therefore, lower doses are necessary in conditions of renal impairment [see Dosage and Administration (2.5)]. The mean elimination half-life of sotalol is 12 hours. Dosing every 12 hours results in trough plasma concentrations that are approximately one-half of those at peak.

Specific Populations

Pediatric: The combined analysis of a single-dose study and a multiple-dose study with 59 children, aged between 3 days and 12 years, showed the pharmacokinetics of sotalol to be first order. A daily dose of 30 mg/m^2 of sotalol was administered in the single dose study and daily doses of 30, 90, and 210 mg/m^2 were administered every 8 hours in the multidose study. After rapid absorption with peak levels occurring on average between 2 to 3 hours following administration, sotalol was eliminated with a mean half-life of 9.5 hours. Steady-state was reached after 1 to 2 days. The average peak to trough concentration ratio was 2. Body surface area was the most important covariate and more relevant than age for the pharmacokinetics of sotalol. The smallest children (BSA<0.33 m^2) exhibited a greater drug exposure (+59%) than the larger children who showed a uniform drug concentration profile. The intersubject variation for oral clearance was 22%.

Geriatric: Age does not significantly alter the pharmacokinetics of Betapace/Betapace AF, but impaired renal function in geriatric patients can increase the terminal elimination half-life, resulting in increased drug accumulation.

Renal Impairment: Sotalol is mainly eliminated via the kidneys through glomerular filtration and to a small degree by tubular secretion. There is a direct relationship between renal function, as measured by serum creatinine or creatinine clearance, and the elimination rate of sotalol. The half-life of sotalol is prolonged (up to 69 hours) in anuric patients. Adjust doses or dosing intervals based on creatinine clearance [see Dosage and Administration (2.5)].

Hepatic Impairment: Patients with hepatic impairment show no alteration in clearance of sotalol.

Drug-Drug Interactions

Antacids: Administration of oral sotalol within 2 hours of antacids may result in a reduction in Cmax and AUC of 26% and 20%, respectively, and consequently in a 25% reduction in the bradycardic effect at rest. Administration of the antacid two hours after oral sotalol has no effect on the pharmacokinetics or pharmacodynamics of sotalol.

No pharmacokinetic interactions were observed with hydrochlorothiazide or warfarin.

13 NONCLINICAL TOXICOLOGY

13.1 Carcinogenesis, Mutagenesis, Impairment of Fertility

Calculations of safety margins are for the maximum recommended human dose (MRHD) of 640 mg/day of sotalol, administered for life-threatening ventricular arrhythmias in a 60-kg human.

No evidence of carcinogenic potential was observed in rats during a 24-month study at 137 to 275 mg/kg/day (approximately 30 times the maximum recommended human oral dose (MRHD) as mg/kg or 5 times the MRHD as mg/m2) or in mice, during a 24-month study at 4141 to 7122 mg/kg/day (approximately 450 to 750 times the MRHD as mg/kg or 36 to 63 times the MRHD as mg/m2).

Sotalol has not been evaluated in any specific assay of mutagenicity or clastogenicity.

14 CLINICAL STUDIES

14.1 Ventricular Arrhythmias

In patients with life-threatening arrhythmias [sustained ventricular tachycardia/fibrillation (VT/VF)], Betapace was studied acutely [by suppression of programmed electrical stimulation (PES) induced VT and by suppression of Holter monitor evidence of sustained VT] and, in acute responders, chronically.

In a double-blind, randomized comparison of Betapace and procainamide in 104 patients given intravenously (total of 2 mg/kg Betapace vs. 19 mg/kg of procainamide over 90 minutes), Betapace suppressed PES induction in 30% of patients vs. 20% for procainamide (P=0.2).

In a randomized clinical trial (Electrophysiologic Study Versus Electrocardiographic Monitoring [ESVEM] Trial) in 486 patients comparing the choice of antiarrhythmic therapy by PES suppression vs. Holter monitor selection (in each case followed by treadmill exercise testing) in patients with a history of sustained VT/VF who were also inducible by PES, the effectiveness acutely and chronically of Betapace was compared with that of 6 other drugs (procainamide, quinidine, mexiletine, propafenone, imipramine, and pirmenol). The Overall response, limited to first randomized drug, was 39% for Betapace and 30% for the pooled other drugs. Acute response rate for first drug randomized using suppression of PES induction was 36% for Betapace vs. a mean of 13% for the pooled other drugs. Using the Holter monitoring endpoint (complete suppression of sustained VT, 90% suppression of NSVT, 80% suppression of PVC pairs, and at least 70% suppression of PVCs), Betapace yielded 41% response vs. 45% for the other drugs combined. Among responders placed on long-term therapy identified acutely as effective (by either PES or Holter), Betapace, when compared to the pool of other drugs, had the lowest two-year mortality (13% vs. 22%), the lowest two-year VT recurrence rate (30% vs. 60%), and the lowest withdrawal rate (38% vs. about 75 to 80%). The most commonly used doses of orally administered Betapace in this trial were 320 to 480 mg/day (66% of patients), with 16% receiving 240 mg/day or less and 18% receiving 640 mg or more.

It cannot be determined, however, in the absence of a controlled comparison of Betapace vs. no pharmacologic treatment (for example, in patients with implanted defibrillators) whether Betapace response causes improved survival or identifies a population with a good prognosis.

Betapace has not been shown to enhance survival in patients with ventricular arrhythmias.

14.2 Supraventricular Arrhythmias

Betapace AF has been studied in patients with symptomatic AFIB/AFL in two principal studies, one in patients with primarily paroxysmal AFIB/AFL, the other in patients with primarily chronic AFIB.

In one study, a U.S. multicenter, randomized, placebo-controlled, double-blind, dose-response trial of patients with symptomatic primarily paroxysmal AFIB/AFL, three fixed dose levels of Betapace AF (80 mg, 120 mg, and 160 mg) twice daily and placebo were compared in 253 patients. In patients with reduced creatinine clearance (40 to 60 mL/min) the same doses were given once daily. Patients were excluded for the following reasons: QT >450 msec; creatinine clearance <40 mL/min; intolerance to beta-blockers; bradycardia-tachycardia syndrome in the absence of an implanted pacemaker; AFIB/AFL was asymptomatic or was associated with syncope, embolic CVA or TIA; acute myocardial infarction within the previous 2 months; congestive heart failure; bronchial asthma or other contraindications to beta-blocker therapy; receiving potassium-losing diuretics without potassium replacement or without concurrent use of ACE-inhibitors; uncorrected hypokalemia (serum potassium <3.5 MEq/L) or hypomagnesemia (serum magnesium <1.5 MEq/L); received chronic oral amiodarone therapy for >1 month within previous 12 weeks; congenital or acquired long QT syndromes; history of Torsade de Pointes with other antiarrhythmic agents, which increase the duration of ventricular repolarization; sinus rate <50 bpm during waking hours; unstable angina pectoris; receiving treatment with other drugs that prolong the QT interval; and AFIB/AFL associated with the Wolff-Parkinson-White (WPW) syndrome. If the QT interval increased to ≥520 msec (or JT ≥430 msec if QRS >100 msec) the drug was discontinued. The patient population in this trial was 64% male, and the mean age was 62 years. No structural heart disease was present in 43% of the patients. Doses were administered once daily in 20% of the patients because of reduced creatinine clearance.

Betapace AF was shown to prolong the time to the first symptomatic, ECG-documented recurrence of AFIB/AFL, as well as to reduce the risk of such recurrences at both 6 and 12 months. The 120 mg dose was more effective than 80 mg, but 160 mg did not appear to have an added benefit. Note that these doses were given twice or once daily, depending on renal function. The results are shown in Figure 1, .

Figure 1: Study 1 – Time to First ECG-Documented Recurrence of Symptomatic AFIB/AFL Since Randomization

Table 3: Study 1 - Patient Status at 12 Months
 | Placebo | Betapace AF Dose
 | Placebo | 80 mg | 120 mg | 160 mg
Randomized | 69 | 59 | 63 | 62
On treatment in NSR at 12 months without recurrencea | 23% | 22% | 29% | 23%
Recurrenceab | 67% | 58% | 49% | 42%
D/C for AEs | 6% | 12% | 18% | 29%
a Symptomatic AFIB/AFL
b Efficacy endpoint of Study 1; study treatment stopped.
Note that columns do not add up to 100% due to discontinuations (D/C) for “other” reasons.

Table 4: Study 1 - Median Time to Recurrence of Symptomatic AFIB/AFL and Relative Risk (vs. Placebo) at 12 Months
 | Placebo n=69 | Betapace AF Dose
 | Placebo n=69 | 80 mg n=59 | 120 mg n=63 | 160 mg n=62
P-value vs. placebo |  | 0.325 | 0.018 | 0.029
Relative Risk (RR) to placebo |  | 0.81 | 0.59 | 0.59
Median time to recurrence (days) | 27 | 106 | 229 | 175

Discontinuation because of adverse events was dose-related.

In a second multicenter, randomized, placebo-controlled, double-blind study of 6 months duration in 232 patients with chronic AFIB, Betapace AF was titrated over a dose range from 80 mg/day to 320 mg/day. The patient population of this trial was 70% male with a mean age of 65 years. Structural heart disease was present in 49% of the patients. All patients had chronic AFIB for >2 weeks but <1 year at entry with a mean duration of 4.1 months. Patients were excluded if they had significant electrolyte imbalance, QTc >460 msec, QRS >140 msec, any degree of AV block or functioning pacemaker, uncompensated cardiac failure, asthma, significant renal disease (estimated creatinine clearance <50 mL/min), heart rate <50 bpm, myocardial infarction or open heart surgery in past 2 months, unstable angina, infective endocarditis, active pericarditis or myocarditis, ≥3 DC cardioversions in the past, medications that prolonged QT interval, and previous amiodarone treatment.

After successful cardioversion patients were randomized to receive placebo (n=114) or Betapace AF (n=118) at a starting dose of 80 mg twice daily. If the initial dose was not tolerated it was decreased to 80 mg once daily, but if it was tolerated, it was increased to 160 mg twice daily. During the maintenance period 67% of treated patients received a dose of 160 mg twice daily, and the remainder received doses of 80 mg once daily (17%) and 80 mg twice daily (16%).

show the results of the trial. There was a longer time to ECG-documented recurrence of AFIB and a reduced risk of recurrence at 6 months compared to placebo.

Table 5: Study 2 - Patient Status at 6 Months
 | Placebo n=114 | Betapace AF n=118
On treatment in NSR at 6 months without recurrencea | 29% | 45%
Recurrenceab | 67% | 49%
D/C for AEs | 3% | 6%
Death | 1%
a Symptomatic or asymptomatic AFIB/AFL
b Efficacy endpoint of Study 2; study treatment stopped.

Table 6: Study 2 - Median Time to Recurrence of Symptomatic AFIB/AFL/Death and Relative Risk (vs. Placebo) at 6 Months
 | Placebo n=114 | Betapace AF n=118 | Relative Risk | P-value
Median time to recurrence (days) | 44 | >180 | 0.55 | 0.002

Figure 2: Study 2 – Time to First ECG-Documented Recurrence of Symptomatic AFIB/AFL/Death Since Randomization

16 HOW SUPPLIED/STORAGE AND HANDLING

Betapace (sotalol hydrochloride); capsule-shaped light-blue scored tablets, imprinted with the strength and “BETAPACE,” are available as follows:

NDC 70515-105-10 80 mg strength, bottle of 100
NDC 70515-109-10 120 mg strength, bottle of 100
NDC 70515-106-10 160 mg strength, bottle of 100

Betapace AF (sotalol hydrochloride); capsule-shaped white scored tablets, imprinted with the strength and “BHCP” are available as follows:

NDC 70515-115-06 80 mg strength, bottle of 60
NDC 70515-119-06 120 mg strength, bottle of 60
NDC 70515-116-06 160 mg strength, bottle of 60

Store at 25°C (77°F); excursions permitted to 15 to 30°C (59 to 86°F) [see USP Controlled Room Temperature].

17 PATIENT COUNSELING INFORMATION

- Advise patients to contact their health care provider in the event of syncope, pre-syncopal symptoms or cardiac palpitations.
- Advise patients that their electrolytes and ECG will be monitored during treatment [see Warnings and Precautions (5.1)].
- Advise patients to contact their healthcare provider in the event of conditions that could lead to electrolyte changes such as severe diarrhea, unusual sweating, vomiting, less appetite than normal, or excessive thirst [see Warnings and Precautions (5.1)].
- Advise patients not to change the Betapace/Betapace AF dose prescribed by their healthcare provider.
- Advise patients that they should not miss a dose, but if they do miss a dose they should not double the next dose to compensate for the missed dose: they should take the next dose at the regularly scheduled time [see Dosage and Administration (2)].
- Advise patients to not interrupt or discontinue Betapace/Betapace AF without their physician’s advice, that they should get their prescription for sotalol filled and refilled on time, so they do not interrupt treatment [see Dosage and Administration (2)].
- Advise patients to not start taking other medications without first discussing new medications with their healthcare provider.
- Advice patients to avoid taking Betapace/Betapace AF within two hours of taking antacids that contain aluminum oxide or magnesium hydroxide [see Drug Interactions (7.7)].
- Inform patients or caregivers that there is a risk of hypoglycemia when Betapace/Betapace AF is given to patients who are fasting or who are vomiting. Inform patients to notify their healthcare provider if they experience symptoms of hypoglycemia. [See Warnings and Precautions (5.7)].

Lactation

- Advise women not to breastfeed while on treatment with Betapace. [see Use in Specific Population (8.2)].

©2023, Covis Pharma. All rights reserved.

Manufactured for:

Covis Pharma
Zug, 6300 Switzerland

PRINCIPAL DISPLAY PANEL - 80 mg BETAPACE

NDC 70515-105-10 100 Tablets

Betapace®
(sotalol HCl)

80 mg

Rx only

COVIS

Each tablet contains
80 mg of sotalol
hydrochloride.

Dosage: See package
insert.

Store at 25°C (77°F);
excursions permitted
to 15-30°C (59-86°F)
[See USP Controlled
Room Temperature].

Dispense in a
well-closed
container (USP).

Mfd for:
Covis Pharma
Zug, 6300
Switzerland

Made in Spain

Rev. 7/19
100414
AC003980 210A0

Batch:
EXP:

PRINCIPAL DISPLAY PANEL - 120 mg BETAPACE

NDC 70515-109-10
100 Tablets

Betapace®
(sotalol HCl)

120 mg

Rx only

COVIS

Each tablet
contains 120 mg
of sotalol
hydrochloride.

Dosage: See
package insert.

Store at 25°C
(77°F); excursions
permitted to
15-30°C (59-86°F)
[See USP
Controlled Room
Temperature].

Dispense in a
well-closed
container (USP).

Mfd for:
Covis Pharma
Zug, 6300
Switzerland

Made in Spain

Rev. 7/19
100415
AC0039120 210A0

Batch:
EXP:

PRINCIPAL DISPLAY PANEL - 160 mg BETAPACE

NDC 70515-106-10
100 Tablets

Betapace®
(sotalol HCl)

160 mg

Rx only

COVIS

Each tablet
contains 160 mg
of sotalol
hydrochloride.

Dosage: See
package insert.

Store at 25°C
(77°F); excursions
permitted to
15-30°C
(59-86°F) [See
USP Controlled
Room
Temperature].

Dispense in a
well-closed
container (USP).

Mfd for:
Covis Pharma
Zug, 6300
Switzerland

Made in Spain

Rev. 7/19
100416
AC0039160 210A0

Batch:
EXP:

PRINCIPAL DISPLAY PANEL - 80 mg BETAPACE AF

NDC 70515-115-06
60 tablets unit of use

BETAPACE AF®
(sotalol HCl)
Patient Pack

80 mg

Rx only

COVIS

Each tablet
contains 80 mg
of sotalol
hydrochloride.

Dosage: Take as
prescribed by your
physician.

Please see
package insert.

Store at 25°C
(77°F); excursions
permitted to
15-30°C (59-86°F)
[See USP
Controlled Room
Temperature].

Mfd for:
Covis Pharma
Zug, 6300
Switzerland

Made in Spain

Rev. 7/19
100417
AC003980 26AF

Batch:
EXP:

PRINCIPAL DISPLAY PANEL - 120 mg BETAPACE AF

NDC 70515-119-06
60 tablets unit of use

BETAPACE AF®
(sotalol HCl)
Patient Pack

120 mg

Rx only

COVIS

Each tablet
contains 120 mg
of sotalol
hydrochloride.

Dosage: Take as
prescribed by your
physician.

Please see
package insert.

Store at 25°C
(77°F); excursions
permitted to
15-30°C (59-86°F)
[See USP
Controlled Room
Temperature].

Mfd for:
Covis Pharma
Zug, 6300
Switzerland

Made in Spain

Rev. 7/19
100419
AC0039120 26AF

Batch:
EXP:

PRINCIPAL DISPLAY PANEL - 160 mg BETAPACE AF

NDC 70515-116-06
60 tablets unit of use

BETAPACE AF®
(sotalol HCl)
Patient Pack

160 mg

Rx only

COVIS

Each tablet
contains 160 mg
of sotalol
hydrochloride.

Dosage: Take as
prescribed by your
physician.

Please see
package insert.

Store at 25°C
(77°F); excursions
permitted to
15-30°C (59-86°F)
[See USP
Controlled Room
Temperature].

Mfd for:
Covis Pharma
Zug, 6300
Switzerland

Made in Spain

Rev. 7/19
100421
AC0039160 26AF

Batch:
EXP: